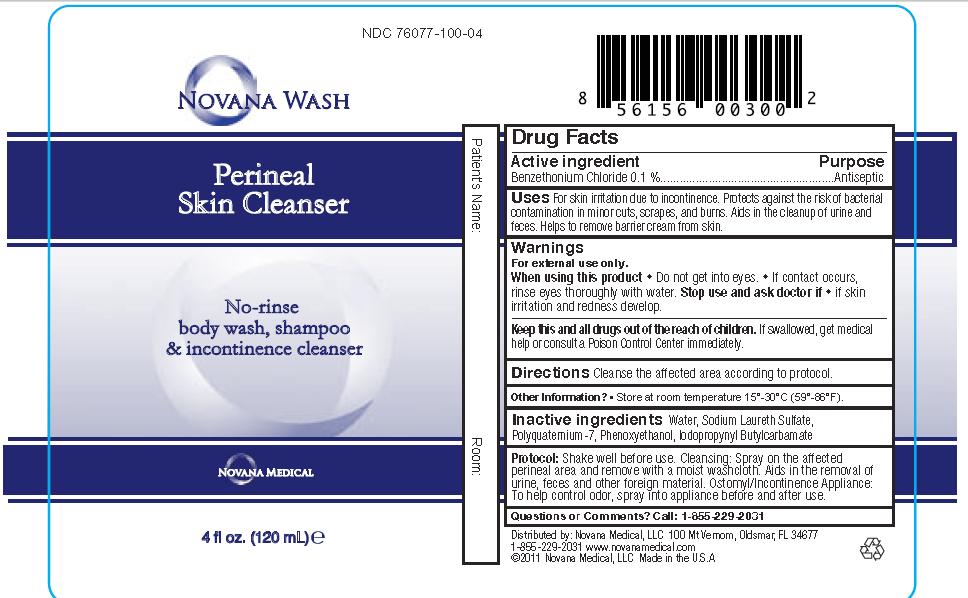 DRUG LABEL: Novana Wash Perineal Skin Cleanser
NDC: 76077-100 | Form: SOLUTION
Manufacturer: NOVANA MEDICAL LLC
Category: otc | Type: HUMAN OTC DRUG LABEL
Date: 20120404

ACTIVE INGREDIENTS: Benzethonium Chloride 0.001 mL/1 mL
INACTIVE INGREDIENTS: Water; Sodium Laureth Sulfate; POLYQUATERNIUM-7 (76/24 ACRYLAMIDE/DADMAC; 120 KD); Phenoxyethanol; Iodopropynyl Butylcarbamate

Drug Facts

Active ingredient Purpose
Benzethonium Chloride 0.1 %......................................................Antiseptic

PURPOSE

Uses For skin irritation due to incontinence. Protects against the risk of bacterial contamination in minor cuts, scrapes, and burns. Aids in the cleanup of urine and feces. Helps to remove barrier cream from skin.

Warnings
For external use only.
When using this product • Do not get into eyes. • If contact occurs, rinse eyes thoroughly with water. Stop use and ask doctor if • if skin irritation and redness develop.

KEEP OUT OF REACH OF CHILDREN

Keep this and all drugs out of the reach of children. If swallowed, get medical help or contact a Poison Control Center right away.

INDICATIONS AND USAGE

Directions Cleanse the affected area according to protocol.

INACTIVE INGREDIENT

Inactive ingredients Water, Sodium Laureth Sulfate, Polyquaternium-7, Phenoxyethanol, Iodopropynyl Butylcarbamate

DOSAGE AND ADMINISTRATION

Protocol: Shake well before use. Cleansing: Spray on the affected perineal area and remove with a moist washcloth. Aids in the removal of urine, feces and other foreign material. Ostomyl/Incontinence Appliance: To help control odor, spray into appliance before and after use.